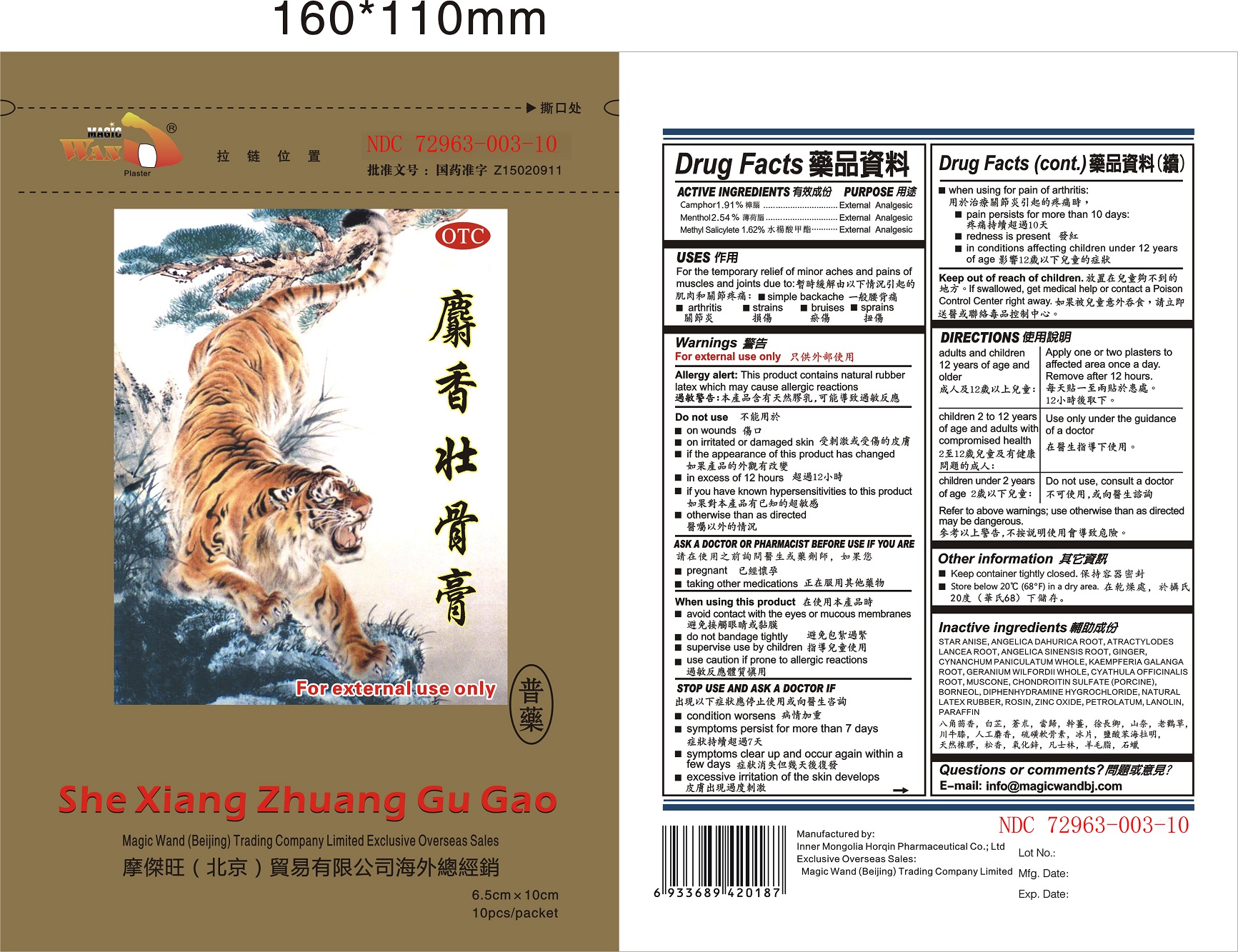 DRUG LABEL: She Xiang Zhuang Gu Gao Regular
NDC: 72963-003 | Form: PLASTER
Manufacturer: Inner Mongolia Horqin Pharmaceutical Co., Ltd
Category: otc | Type: HUMAN OTC DRUG LABEL
Date: 20190325

ACTIVE INGREDIENTS: CAMPHOR (SYNTHETIC) 1.91 g/100 g; MENTHOL 2.54 g/100 g; METHYL SALICYLATE 1.62 g/100 g
INACTIVE INGREDIENTS: STAR ANISE; ANGELICA DAHURICA ROOT; ATRACTYLODES LANCEA ROOT; ANGELICA SINENSIS ROOT; GINGER; CYNANCHUM PANICULATUM WHOLE; KAEMPFERIA GALANGA ROOT; GERANIUM WILFORDII WHOLE; CYATHULA OFFICINALIS ROOT; MUSCONE; CHONDROITIN SULFATE (PORCINE); BORNEOL; DIPHENHYDRAMINE HYDROCHLORIDE; NATURAL LATEX RUBBER; ROSIN; ZINC OXIDE; PETROLATUM; LANOLIN; PARAFFIN

Inner Mongolia Horqin Pharmaceutical Co., Ltd

ACTIVE INGREDIENTS

Camphor 1.91%

Menthol 2.54%

Methyl Salicylete 1.62%

PURPOSE

Camphor External Analgesic

Menthol External Analgesic

Methyl Salicylate External Analgesic

USES

For the temporary relief of minor aches and pains of muscles and joints due to:

simple backache

arthritis

strains

bruises

sprains

Warnings

For External Use only.

Allergy Alert: This product contains natural rubber latex which may cause allergic reactions.

Do not use

on wounds

on irritated or damaged skin

if the appearance of this product has changed

in excess of 12 hours

if you have known hypersensitive to this product

otherwise than as directed

ASK A DOCTOR OR PHARMACIST BEFORE USE IF YOU ARE

pregnant

taking other medications

When using this product

avoid contact with the eye or mucous membranes

do not bandage tightly

supervise use by children

use caution if prone to allergic reactions

STOP USE AND ASK A DOCTOR IF

condition worsens

symptoms persist for more than 7 days

symptoms clear up and occur again within a few days

excessive irritation of the skin develops

when using for pain of arthritis

pain persists for more than 10 days

redness is present

in conditions affecting children under 12 years of age

Keep out of reach of children.

If swallowed, get medical help or contact a Poison Control Center right away.

DIRECTIONS

Adults and children 12 years of age and older: Apply one or two plasters to affected area once a day. Remove after 12 hours.
Children 2 to 12 years of age and adults with compromised health: Use only under the guidance of a doctor.
Children under 2 years of age: Do not use, consult a doctor.
Refer to the above warnings: use otherwise than as directed may be dangerous.

Other Information

Keep container tightly closed.

Store below 20ºC (68°F) in a dry area.

Inactive Ingredients

STAR ANISE, ANGELICA DAHURICA ROOT, ATRACTYLODES LANCEA ROOT, ANGELICA SINENSIS ROOT, GINGER, CYNANCHUM PANICULATUM WHOLE, KAEMPFERIA GALANGA ROOT, GERANIUM WILFORDII WHOLE, CYATHULA OFFICINALIS ROOT, MUSCONE, CHONDROITIN SULFATE (PORCINE), BORNEOL, DIPHENHYDRAMINE HYGROCHLORIDE, NATURAL LATEX RUBBER, ROSIN, ZINC OXIDE, PETROLATUM, LANOLIN, PARAFFIN

Questions or Comments?

E-mail: info@magicwandbj.com

Exclusive Overseas Sales

Magic Wand (Beijing) Trading Company Limited